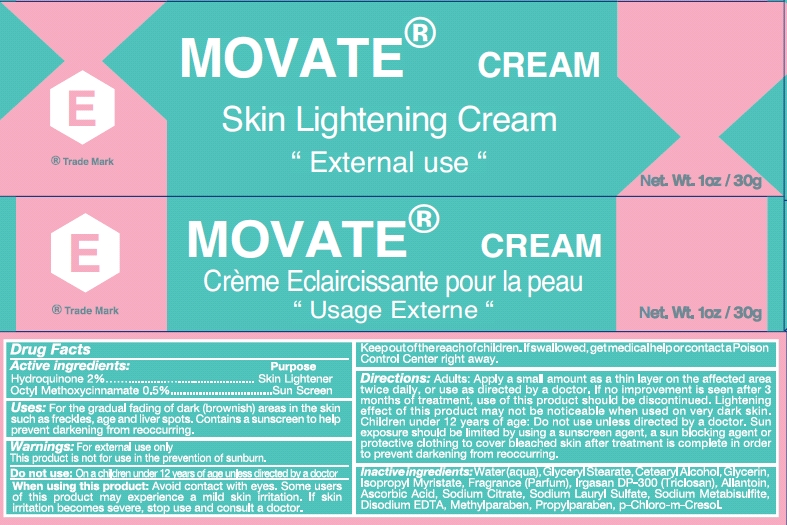 DRUG LABEL: Movate Skin Lightening
NDC: 66129-140 | Form: CREAM
Manufacturer: International Beauty Exchange
Category: otc | Type: HUMAN OTC DRUG LABEL
Date: 20110513

ACTIVE INGREDIENTS: HYDROQUINONE .6 g/30 g; OCTINOXATE .15 g/30 g
INACTIVE INGREDIENTS: WATER; GLYCERYL STEARATE CITRATE; CETOSTEARYL ALCOHOL; GLYCERIN; ISOPROPYL MYRISTATE; TRICLOSAN; ALLANTOIN; ASCORBIC ACID; SODIUM METABISULFITE; SODIUM CITRATE; SODIUM LAURYL SULFATE; EDETATE DISODIUM; METHYLPARABEN; PROPYLPARABEN; CHLOROCRESOL

Drug Facts

ACTIVE INGREDIENT

Hydroquinone 2%
Ethylhexyl Methoxycinnamate (Octyl Methoxycinnamate) 0.5%

WARNINGS

For external use only

PURPOSE

Skin Lightener

WHEN USING

Avoid contact with the eyes

DO NOT USE

On children under 12 years of age unless directed by a doctor

KEEP OUT OF REACH OF CHILDREN

If swallowed, get medical help or contact a Poison Control center right away